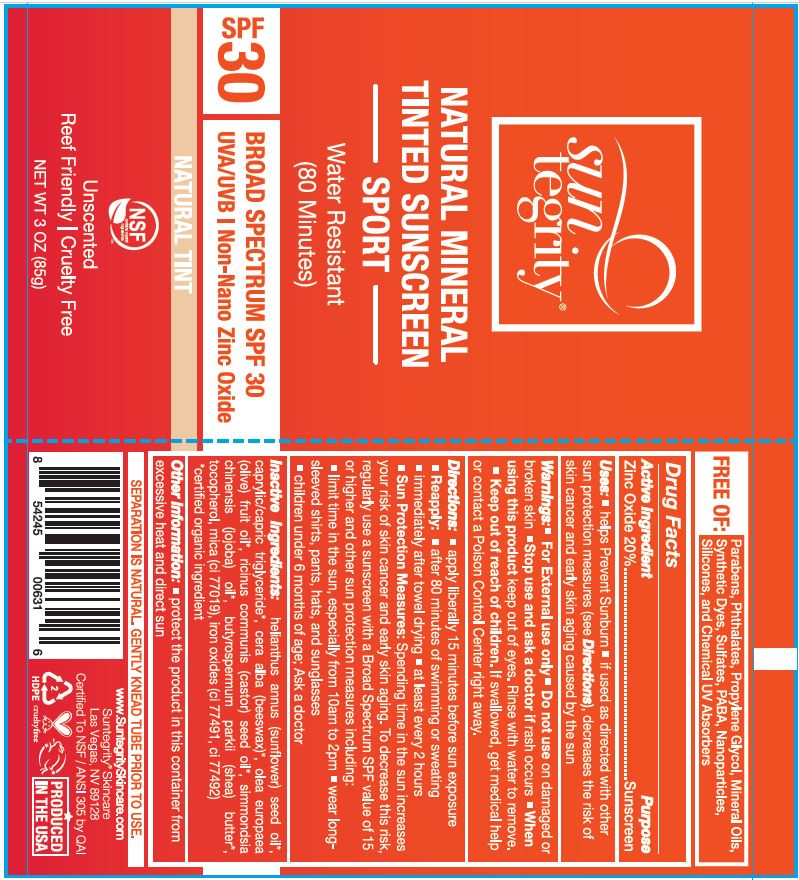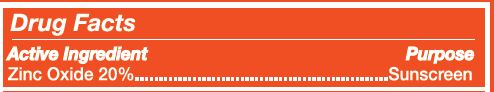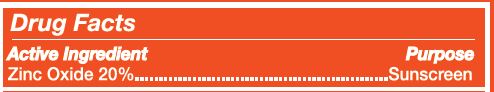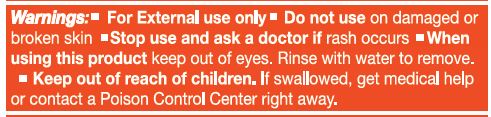 DRUG LABEL: SUNSCREEN
NDC: 62932-246 | Form: OINTMENT
Manufacturer: Private Label Select Ltd CO
Category: otc | Type: HUMAN OTC DRUG LABEL
Date: 20201231

ACTIVE INGREDIENTS: ZINC OXIDE 20 g/100 g
INACTIVE INGREDIENTS: SHEA BUTTER; .ALPHA.-TOCOPHEROL, D-; MICA; MEDIUM-CHAIN TRIGLYCERIDES; FERRIC OXIDE RED; FERROSOFERRIC OXIDE; WHITE WAX; SUNFLOWER OIL; CASTOR OIL; OLIVE OIL; JOJOBA OIL; FERRIC OXYHYDROXIDE; .DELTA.-TOCOPHEROL; .GAMMA.-TOCOPHEROL; .BETA.-TOCOPHEROL

Suntegrity Natural Mineral Tinted Sunscreen Sport, Natural Tint